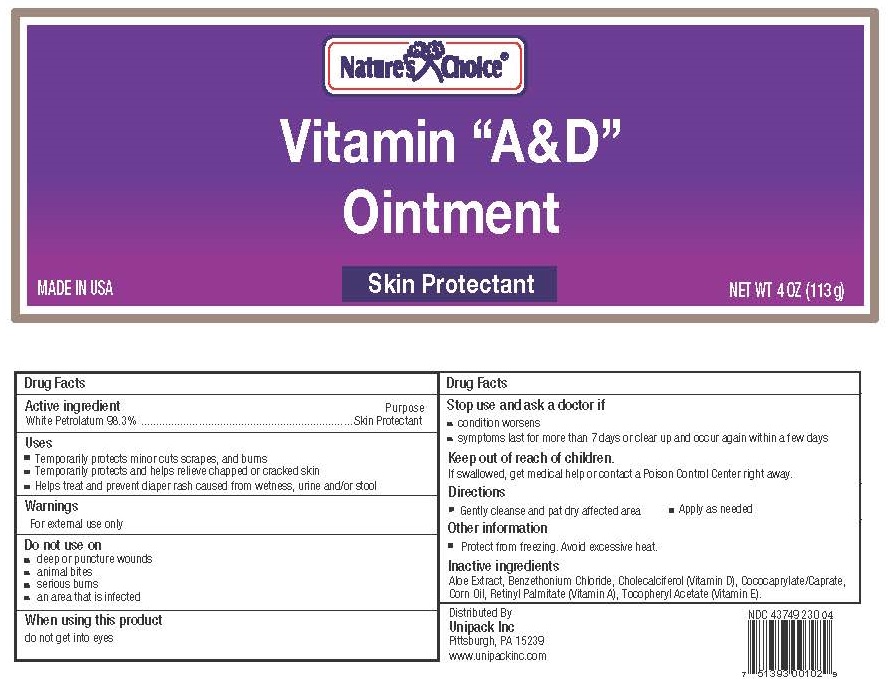 DRUG LABEL: Natures Choice Vitamins A and D
NDC: 43749-230 | Form: OINTMENT
Manufacturer: Unipack, Inc.
Category: otc | Type: HUMAN OTC DRUG LABEL
Date: 20180115

ACTIVE INGREDIENTS: PETROLATUM 99.397 g/100 g
INACTIVE INGREDIENTS: ALOE VERA LEAF 0.5 g/100 g; VITAMIN A PALMITATE .002 g/100 g; CHOLECALCIFEROL .001 g/100 g; .ALPHA.-TOCOPHEROL ACETATE, DL- .1 g/100 g

Active Ingredient:

Active Ingredient: Purpose

Petrolatum USP 99%............................................................................Skin Protectant

Inactive ingredients:

aloe extract, cholecalciferol (vitamin D), retinyl palmitate (vitamin A), tocopheryl acetate (vitamin E)

Purpose

Skin Protectant

Uses

Temporarily protects minor: cuts - scrapes - burns

Temporarily protects and helps relieve chapped or cracked skin

Helps protect against the drying effects of wind and cold weather

Warning

For external use only

Do not use on - deep or puncture wounds - Animals bites - Serious burns

When using this product - do not get into eyes

Stop use and ask a doctor if - condition worsens - symptoms last more than 7 days or clear up and occur again within a few days

Keep out of reach of children

if swallowed, get medical help or contact a Poison Control Center right away

Directions

apply as needed